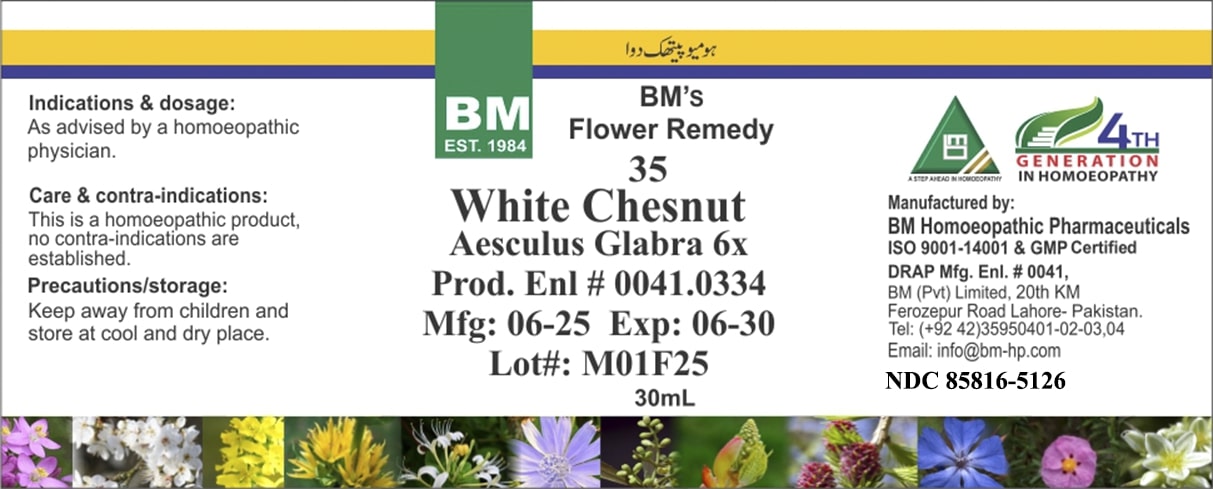 DRUG LABEL: BM White Chesnut
NDC: 85816-5126 | Form: LIQUID
Manufacturer: BM Private Limited
Category: homeopathic | Type: HUMAN OTC DRUG LABEL
Date: 20250701

ACTIVE INGREDIENTS: HORSE CHESTNUT 6 [hp_X]/1 mL
INACTIVE INGREDIENTS: ALCOHOL 0.985 mL/1 mL

BM White Chesnut 6X

INACTIVE INGREDIENT

ALCOHOL

ACTIVE INGREDIENT

White Chestnut

Indications & dosage: As advised by a homoeopathic physician.

Indications & dosage: As advised by a homoeopathic physician.

PURPOSE

Indications & dosage: As advised by a homoeopathic physician.

CONTRAINDICATIONS

Care & contra-indications: This is a homoeopathic product, no contra-indications are established.

WARNINGS

Precautions/storage: Keep away from children and store at cool and dry place.

KEEP OUT OF REACH OF CHILDREN

Precautions/storage: Keep away from children and store at cool and dry place.

STORAGE AND HANDLING

Precautions/storage: Keep away from children and store at cool and dry place.

Entire package label